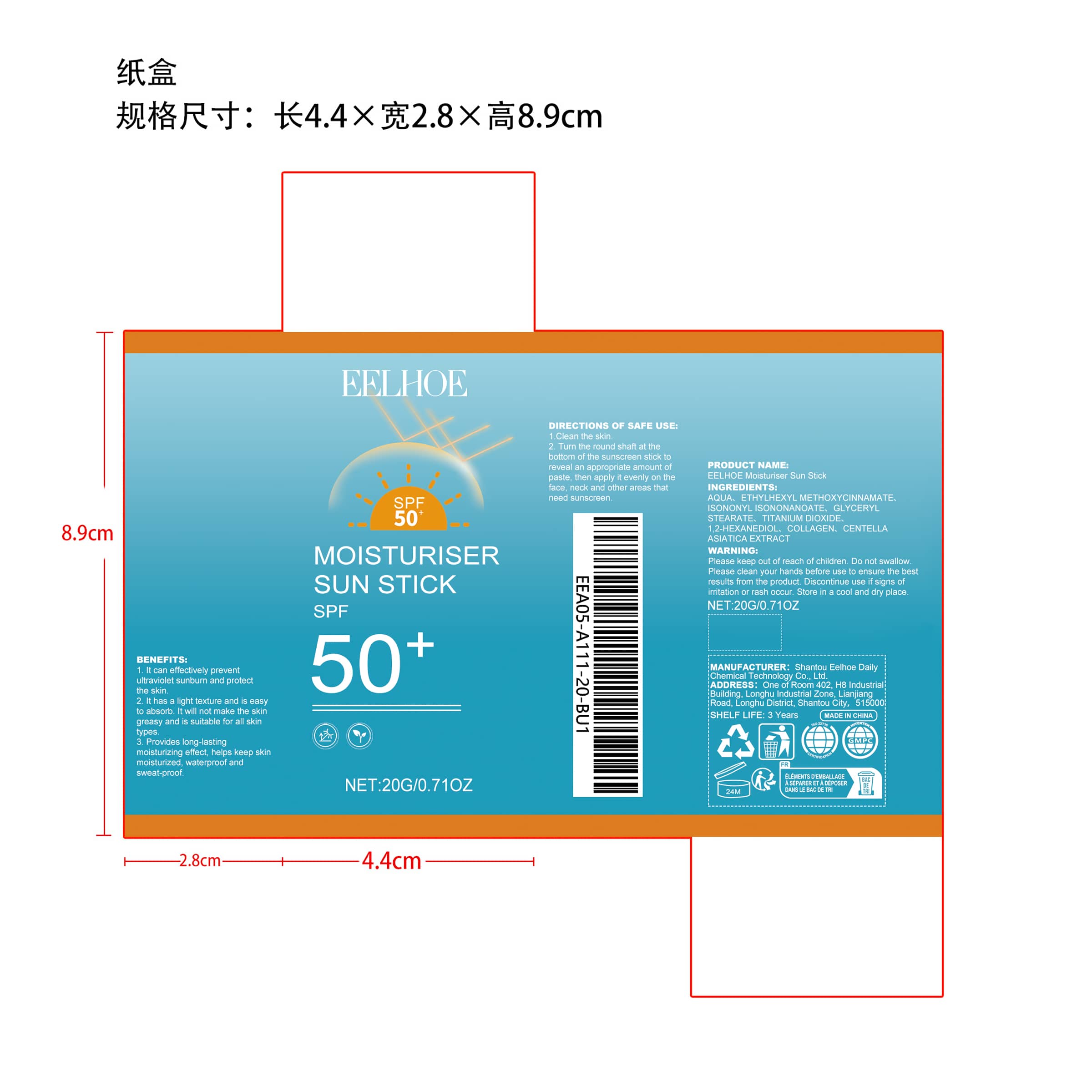 DRUG LABEL: EELHOE Moisturiser Sun Stick
NDC: 85064-024 | Form: CREAM
Manufacturer: Shantou Eelhoe Daily Chemical Technology Co., Ltd.
Category: otc | Type: HUMAN OTC DRUG LABEL
Date: 20251206

ACTIVE INGREDIENTS: CENTELLA ASIATICA 0.004 mg/20 mg
INACTIVE INGREDIENTS: 1,2-HEXANEDIOL 0.06 mg/20 mg; ETHYLHEXYL METHOXYCINNAMATE 1 mg/20 mg; ISONONYL ISONONANOATE 0.8 mg/20 mg; COLLAGEN ALPHA-1(I) CHAIN BOVINE 0.004 mg/20 mg; GLYCERYL STEARATE 0.3 mg/20 mg; AQUA 17.632 mg/20 mg; TITANIUM DIOXIDE 0.2 mg/20 mg

ACTIVE INGREDIENT

CENTELLA ASIATICA EXTRACT

PURPOSE

1. It can effectively prevent ultraviolet sunburn and protect the skin.

2. It has a light texture and is easy to absorb. It will not make the skin greasy and is suitable for all skin types.

3. Provides long-lasting moisturizing effect, helps keep skin moisturized, waterproof and sweat-proof.

WHEN USING

1.Clean the skin.

2. Turn the round shaft at the bottom of the sunscreen stick to reveal an appropriate amount of paste, then apply it evenly on the face, neck and other areas that need sunscreen.

WARNINGS

Please keep out of reach of children. Do not swallow.Please clean your hands before use to ensure the best results from the product. Discontinue use if signs of irritation or rash occur. Store in a cool and dry place.

DO NOT USE

Discontinue use if signs of irritation or rash occur.

STOP USE

Discontinue use if signs of irritation or rash occur.

KEEP OUT OF REACH OF CHILDREN

Please keep out of reach of children. Do not swallow.

STORAGE AND HANDLING

Store in a cool and dry place.

INACTIVE INGREDIENT

AQUA、ETHYLHEXYL METHOXYCINNAMATE、ISONONYL ISONONANOATE、GLYCERYL STEARATE、TITANIUM DIOXIDE、1,2-HEXANEDIOL、COLLAGEN

INDICATIONS AND USAGE

1.Clean the skin.

2. Turn the round shaft at the bottom of the sunscreen stick to reveal an appropriate amount of paste, then apply it evenly on the face, neck and other areas that need sunscreen.

DOSAGE AND ADMINISTRATION

1.Clean the skin.

2. Turn the round shaft at the bottom of the sunscreen stick to reveal an appropriate amount of paste, then apply it evenly on the face, neck and other areas that need sunscreen.